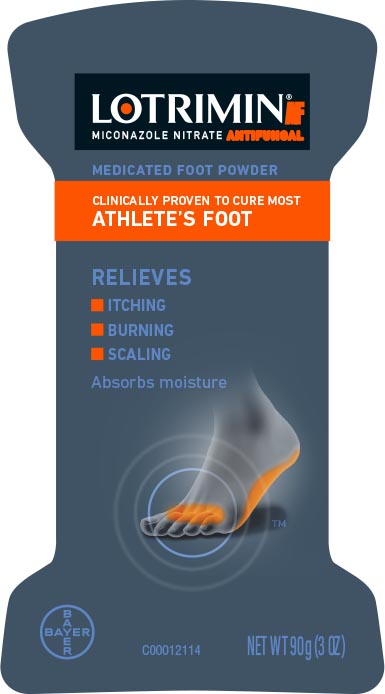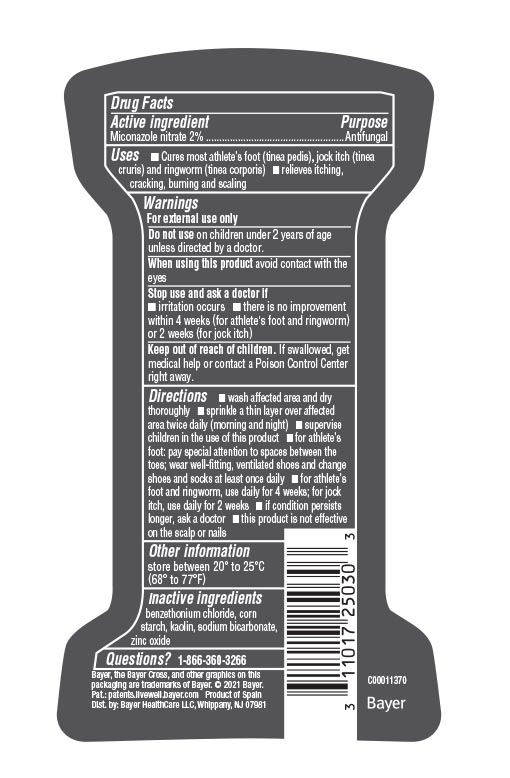 DRUG LABEL: Lotrimin
NDC: 11523-0919 | Form: POWDER
Manufacturer: Bayer HealthCare LLC.
Category: otc | Type: HUMAN OTC DRUG LABEL
Date: 20260116

ACTIVE INGREDIENTS: MICONAZOLE NITRATE 20 mg/1 g
INACTIVE INGREDIENTS: BENZETHONIUM CHLORIDE; STARCH, CORN; KAOLIN; SODIUM BICARBONATE; ZINC OXIDE

Lotrimin®
Antifungal

Drug Facts

Active ingredient

Miconazole nitrate 2%

Purpose

Antifungal

Uses

- Cures most athlete's foot (tinea pedis), jock itch (tinea cruris) and ringworm (tinea corporis)
- relieves itching, cracking, burning and scaling

Warnings

For external use only

Do not use on children under 2 years of age unless directed by a doctor.

When using this product

avoid contact with the eyes

Stop use and ask a doctor if

- irritation occurs
- if there is no improvement within 4 weeks (for athlete's foot and ringworm) or 2 weeks (for jock itch)

Keep out of reach of children. If swallowed, get medical help or contact a Poison Control Center right away.

Directions

- wash affected area and dry thoroughly
- sprinkle a thin layer over affected area twice daily (morning and night)
- supervise children in the use of this product
- for athlete's foot: pay special attention to spaces between the toes; wear well-fitting, ventilated shoes and change shoes and socks at least once daily
- for athlete's foot and ringworm, use daily for 4 weeks; for jock itch, use daily for 2 weeks
- if condition persists longer, ask a doctor
- this product is not effective on the scalp or nails

Other information

store between 20° to 25°C (68° to 77°F)

Inactive ingredients

benzethonium chloride, corn starch, kaolin, sodium bicarbonate, starch/acrylates/acrylamide copolymer, zinc oxide

PRINCIPAL DISPLAY PANEL - 90g Can Label

NDC 11523-0919-1

LOTRIMIN® AF
ANTIFUNGAL
miconazole nitrate

Cures Most
Athlete's Foot

POWDER

- Absorbs Moisture
- Relieves Itching,
  Burning & Scaling

NET WT 90g (3 OZ)

37871-00